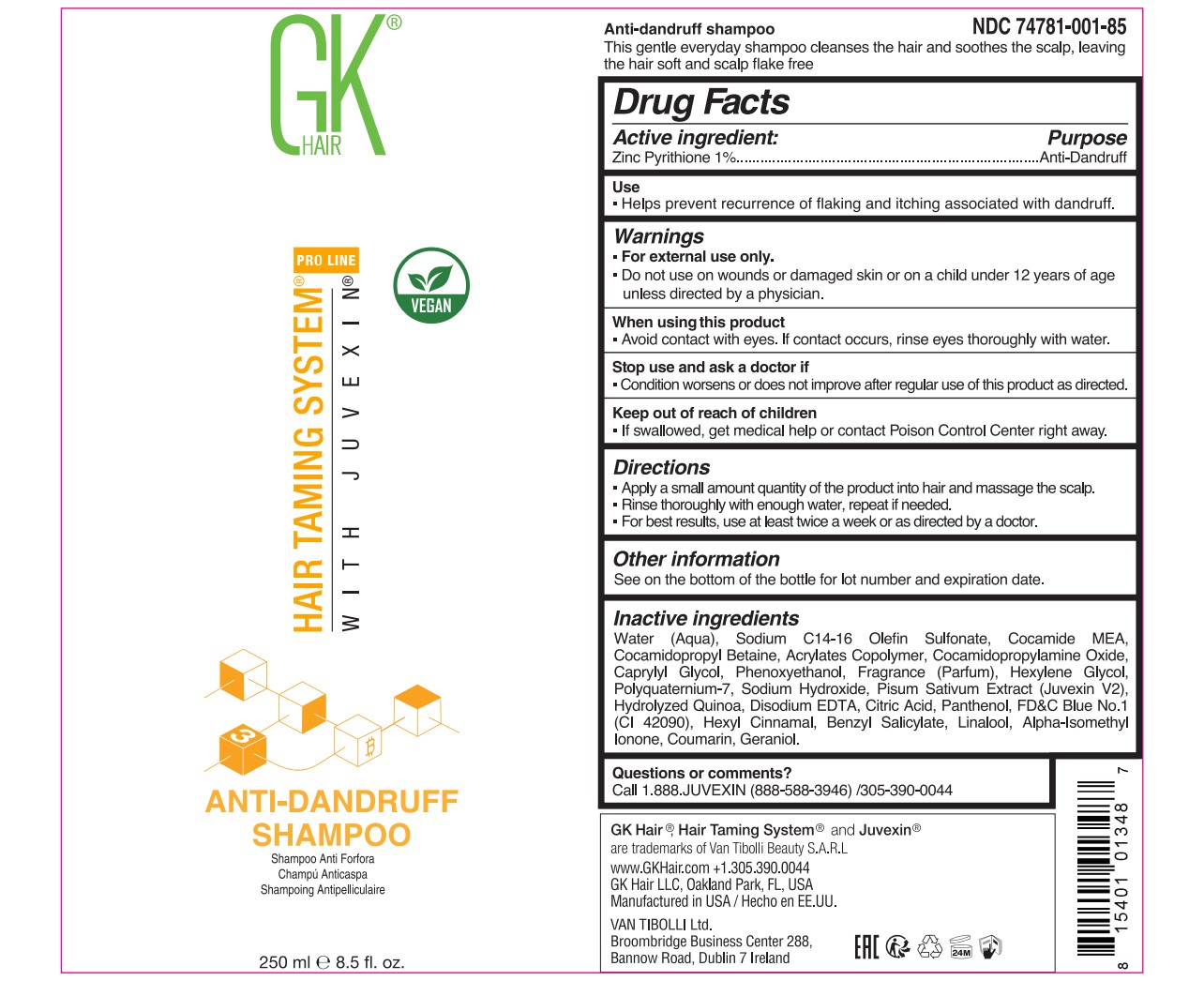 DRUG LABEL: GK HAIR ANTI-DANDRUFF
NDC: 74781-001 | Form: SHAMPOO
Manufacturer: Tibolli LLC
Category: otc | Type: HUMAN OTC DRUG LABEL
Date: 20240820

ACTIVE INGREDIENTS: PYRITHIONE ZINC 1 g/100 mL
INACTIVE INGREDIENTS: ISOMETHYL-.ALPHA.-IONONE; COCO MONOETHANOLAMIDE; .ALPHA.-HEXYLCINNAMALDEHYDE; COCAMIDOPROPYLAMINE OXIDE; ANHYDROUS CITRIC ACID; SODIUM HYDROXIDE; WATER; SODIUM C14-16 OLEFIN SULFONATE; PHENOXYETHANOL; FD&C BLUE NO. 1; LINALOOL, (+)-; BENZYL SALICYLATE; COUMARIN; PANTHENOL; GERANIOL; COCAMIDOPROPYL BETAINE; CAPRYLYL GLYCOL; HEXYLENE GLYCOL; EDETATE DISODIUM; POLYQUATERNIUM-7 (70/30 ACRYLAMIDE/DADMAC; 1600 KD); PISUM SATIVUM (PEA) EXTRACT; CHENOPODIUM QUINOA SEEDCAKE

74781-001-85

ACTIVE INGREDIENT

Zinc Pyrithione 1%

PURPOSE

Anti-Dandruff

INDICATIONS AND USAGE

Helps prevent recurrence of flaking and itching associated with dandruff.

WARNINGS

For external use only.

Do not use on wounds or damaged skin or on a child under 12 years of age unless directed by a physician

WHEN USING

Avoid contact with the eyes. If contact occurs, rinse eyes thoroughly with water.

STOP USE

Conditions worsens or does not improve after regular use of this product as directed.

KEEP OUT OF REACH OF CHILDREN

If swallowed, get medical help or contact Poison Control Center right away.

DOSAGE AND ADMINISTRATION

Apply a small amount quantity of the product into hair and massage the scalp.

Rinse thoroughly with enough water, repeat if needed.

For best results, use at least twice a week or as directed by a doctor.

OTHER SAFETY INFORMATION

See on the bottom of the bottle for lot number and expiration date.

INACTIVE INGREDIENT

Water (Aqua), Sodium C14-16 Olefin Sulfonate, Cocamide MEA, Cocamidopropyl Betaine, Acrylates Copolymer, Cocamidopropylamine Oxide, Caprylyl Glycol, Phenoxyethanol, Fragrance (Parfum), Hexylene Glycol, Polyquaternium-7, Sodium Hydroxide, Pisum Sativum Extract (Juvexin V2), Hydrolyzed Quinoa, Disodium EDTA, Citric Acid, Panthenol, FD&C Blue No.1 (CI 42090), Hexyl Cinnamal, Benzyl Salicylate, Linalool, Alpha-Isomethyl Ionone, Coumarin, Geraniol.

QUESTIONS OR COMMENTS?

Call: 1.888.JUVEXIN (888-588-3946) /305-390-0044